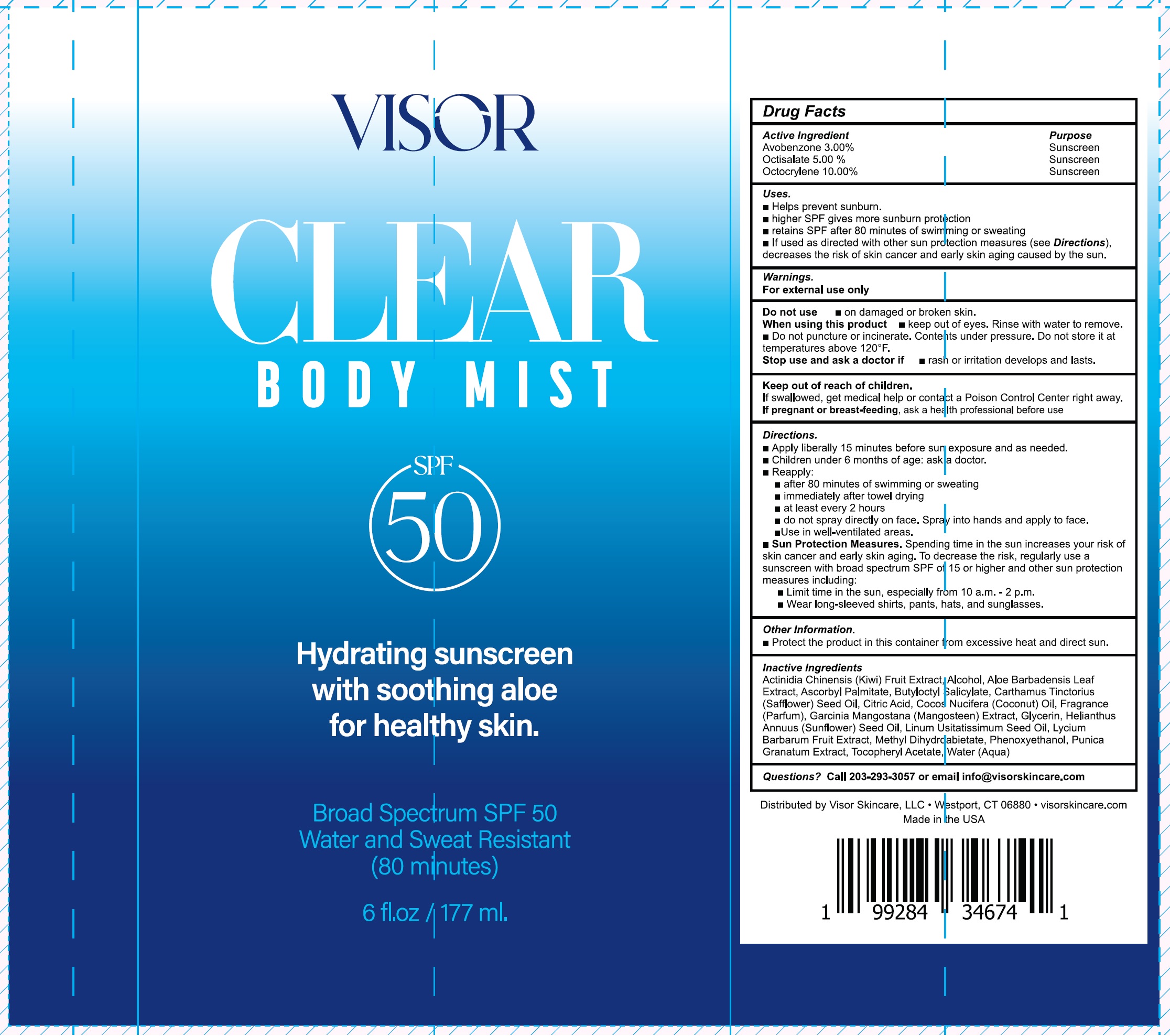 DRUG LABEL: Visor Clear Body Mist Hydrating Sunscreen SPF 50
NDC: 85335-597 | Form: LIQUID
Manufacturer: VISOR SKINCARE LLC
Category: otc | Type: HUMAN OTC DRUG LABEL
Date: 20250505

ACTIVE INGREDIENTS: AVOBENZONE 30 mg/1 mL; OCTISALATE 50 mg/1 mL; OCTOCRYLENE 100 mg/1 mL
INACTIVE INGREDIENTS: KIWI FRUIT; ALCOHOL; ALOE VERA LEAF; ASCORBYL PALMITATE; BUTYLOCTYL SALICYLATE; SAFFLOWER OIL; CITRIC ACID MONOHYDRATE; COCONUT OIL; GLYCERIN; SUNFLOWER OIL; LYCIUM BARBARUM FRUIT; METHYL DIHYDROABIETATE; PHENOXYETHANOL; PUNICA GRANATUM ROOT BARK; .ALPHA.-TOCOPHEROL ACETATE; WATER

Visor Clear Body Mist Hydrating Sunscreen SPF 50

Active Ingredient

Avobenzone, 3.00%
Octisalate 5.00%
Octocrylene 10.00%

Purpose

Sunscreen

Uses.

- Helps prevent sunburn.
- higher SPF gives more sunburn protection
- retains SPF after 80 minutes of swimming or sweating
- If used as directed with other sun protection measures (see Directions), decreases the risk of skin cancer and early skin agingcaused by the sun.

Warnings.

For external use only

Do not use

- on damaged or broken skin.

When using this product

- keep out of eyes. Rinse with water to remove.
- Do not puncture or incinerate. Contents under pressure. Do not store it at temperatures above 120°F.

Stop use and ask a doctor if

- rash or irritation develops and lasts.

Keep out of reach of children.

If swallowed, get medical help or contact a Poison Control Center right away.

If pregnant or breast-feeding,

ask a health professional before use

Directions.

- Apply liberally 15 minutes before sun exposure and as needed.
- Children under 6 months of age: ask a doctor.
- Reapply:
- after 80 minutes of swimming or sweating
- immediately after towel drying
- at least every 2 hours
- do not spray directly on face. Spray into hands and apply to face.
- Use in well-ventilated areas.
- Sun Protection Measures.Spending time in the sun increase your risk of skin cancer and early skin aging. To decrease this risk, regularly use a sunscreen with a broad spectrum SPF of 15 or higher and other sun protection measures including:
- Limit time in the sun, especially from 10 a.m.-2p.m.
- Wear long-sleeved shirts, pants,hats,and sunglasses.

Other information.

- Protect the product in this container from excessive heat and direct sun.

Inactive Ingredients

Actinidia Chinensis (Kiwi) Fruit Extract, Alcohol, Aloe Barbadensis Leaf Extract, Ascorbyl Palmitate, Butyloctyl Salicylate, Carthamus Tinctorius (Safflower) Seed Oil, Citric Acid, Cocos Nucifera (Coconut) Oil, Fragrance (Parfum), Garcinia Mangostana (Mangosteen) Extract, Glycerin, Helianthus Annuus (Sunflower) Seed Oil, Linum Usitatissimum Seed Oil, Lycium Barbarum Fruit Extract, Methyl Dihydroabietate, Phenoxyethanol, Punica Granatum Extract, Tocopheryl Acetate, Water (Aqua)

undefined

Call 203-293-3057 or email info@visorskincare.com